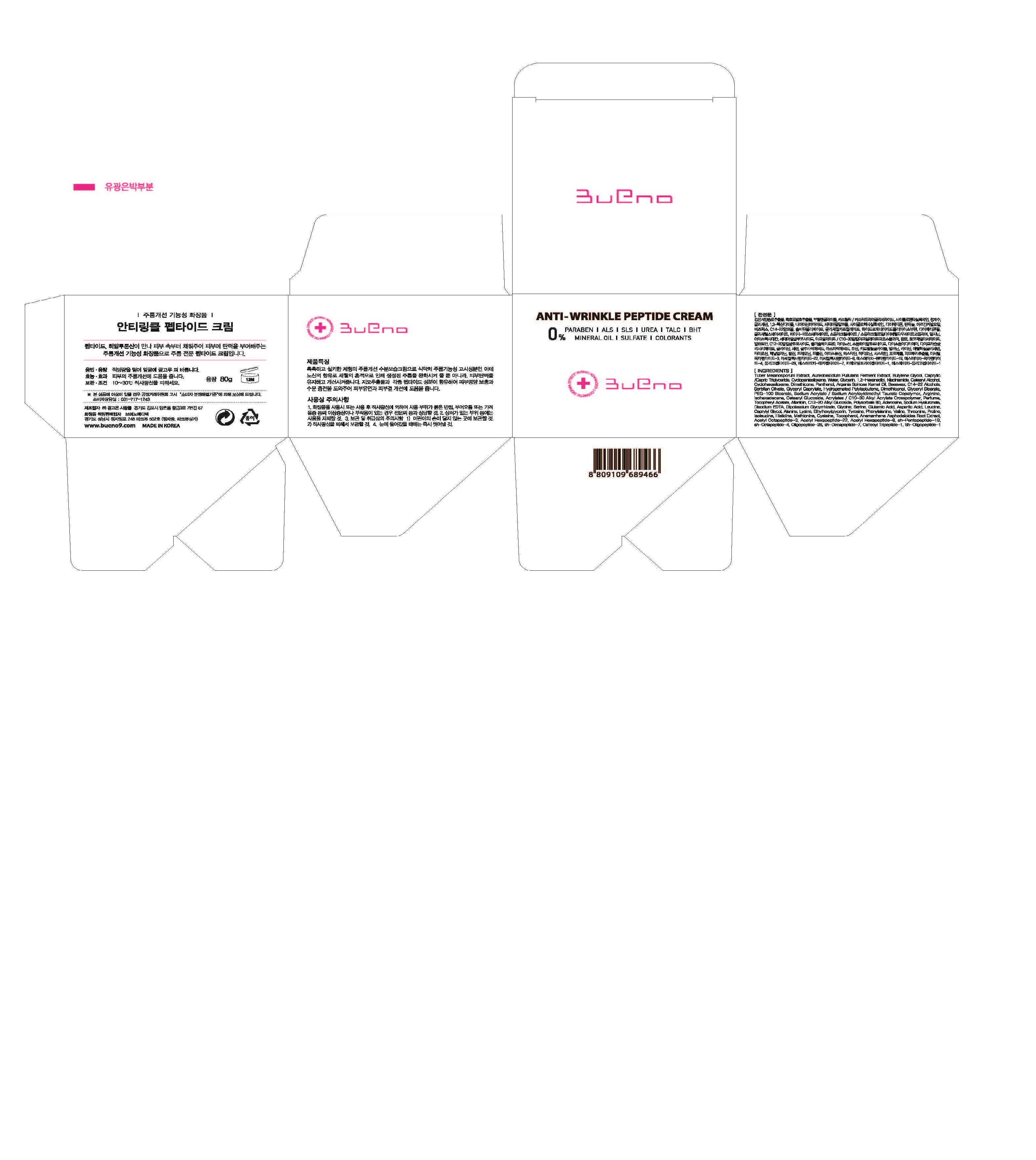 DRUG LABEL: BUENO ANTI-WRINKLE PEPTIDE
NDC: 73261-0002 | Form: CREAM
Manufacturer: Bueno MEDITECH
Category: otc | Type: HUMAN OTC DRUG LABEL
Date: 20190803

ACTIVE INGREDIENTS: GLYCERIN 3 g/100 g
INACTIVE INGREDIENTS: NIACINAMIDE

Drug Facts

ACTIVE INGREDIENT

glycerin

INACTIVE INGREDIENT

Tuber Melanosporum Extract
Aureobasidium Pullulans Ferment Extract
Butylene Glycol
Caprylic/Capric Triglyceride
Cyclopentasiloxane
Water
Glycerin
1,2-Hexanediol
Niacinamide
Cetearyl Alcohol
Cyclohexasiloxane
Dimethicone
Panthenol
Argania Spinosa Kernel Oil
Beeswax
C14-22 Alcohols
Sorbitan Olivate
Glyceryl Caprylate
Hydrogenated Polyisobutene
Dimethiconol
Glyceryl Stearate
PEG-100 Stearate
Sodium Acrylate/Sodium Acryloyldimethyl Taurate Copolymer
Arginine
Isohexadecane
Cetearyl Glucoside
Acrylates/C10-30 Alkyl Acrylate Crosspolymer
Perfume
Tocopheryl Acetate
Allantoin
C12-20 Alkyl Glucoside
Polysorbate 80
Adenosine
Sodium Hyaluronate
Disodium EDTA
Dipotassium Glycyrrhizate
Glycine
Serine
Glutamic Acid
Aspartic Acid
Leucine
Caprylyl Glycol
Alanine
Lysine
Ethylhexylglycerin
Tyrosine
Phenylalanine
Valine
Threonine
Proline
Isoleucine
Histidine
Methionine
Cysteine
Tocopherol
Anemarrhena Asphodeloides Root Extract
Acetyl Octapeptide-3
Acetyl Hexapeptide-22
Acetyl Hexapeptide-8
sh-Pentapeptide-19
sh-Octapeptide-4
Oligopeptide-28
sh-Decapeptide-7
Caffeoyl Tripeptide-1
Sh-Oligopeptide-1

PURPOSE

anti-wrinkle

keep out of reach of the children

INDICATIONS AND USAGE

apply proper amount to the skin

WARNINGS

discontinue use if irritation or rash appears

avoid using on injured skin

keep out of childres

store out of direct sunlight

DOSAGE AND ADMINISTRATION

for topical use only